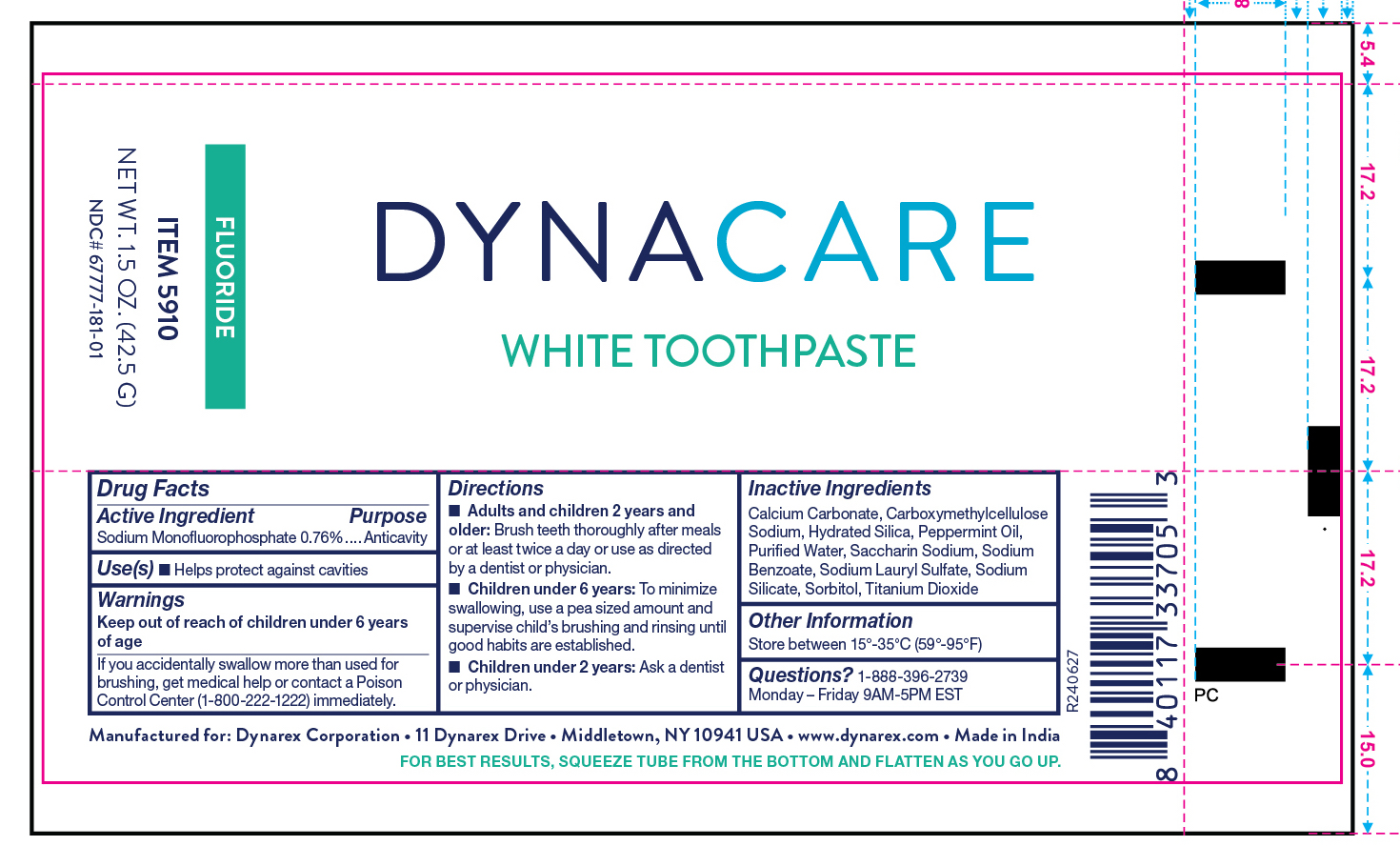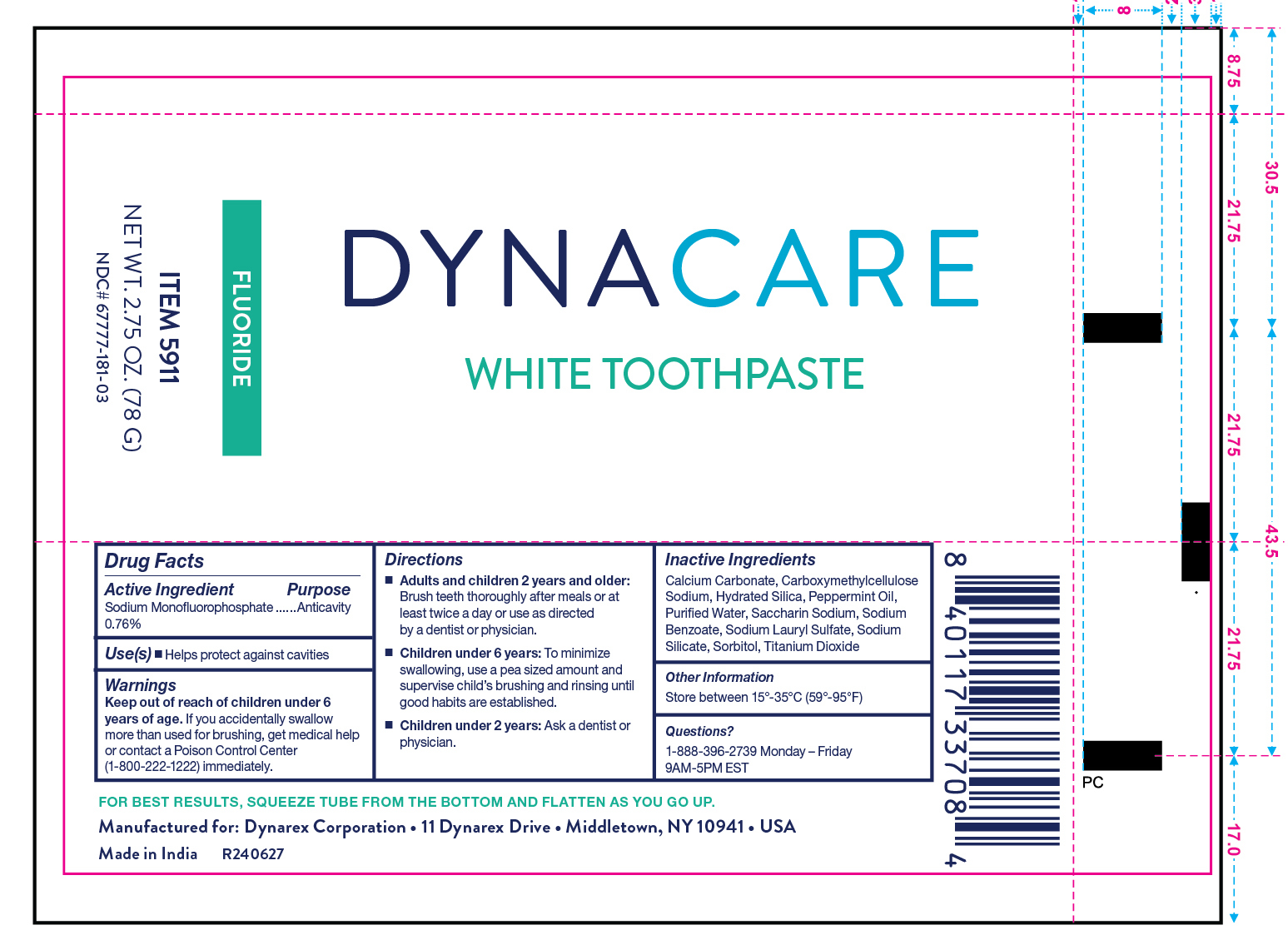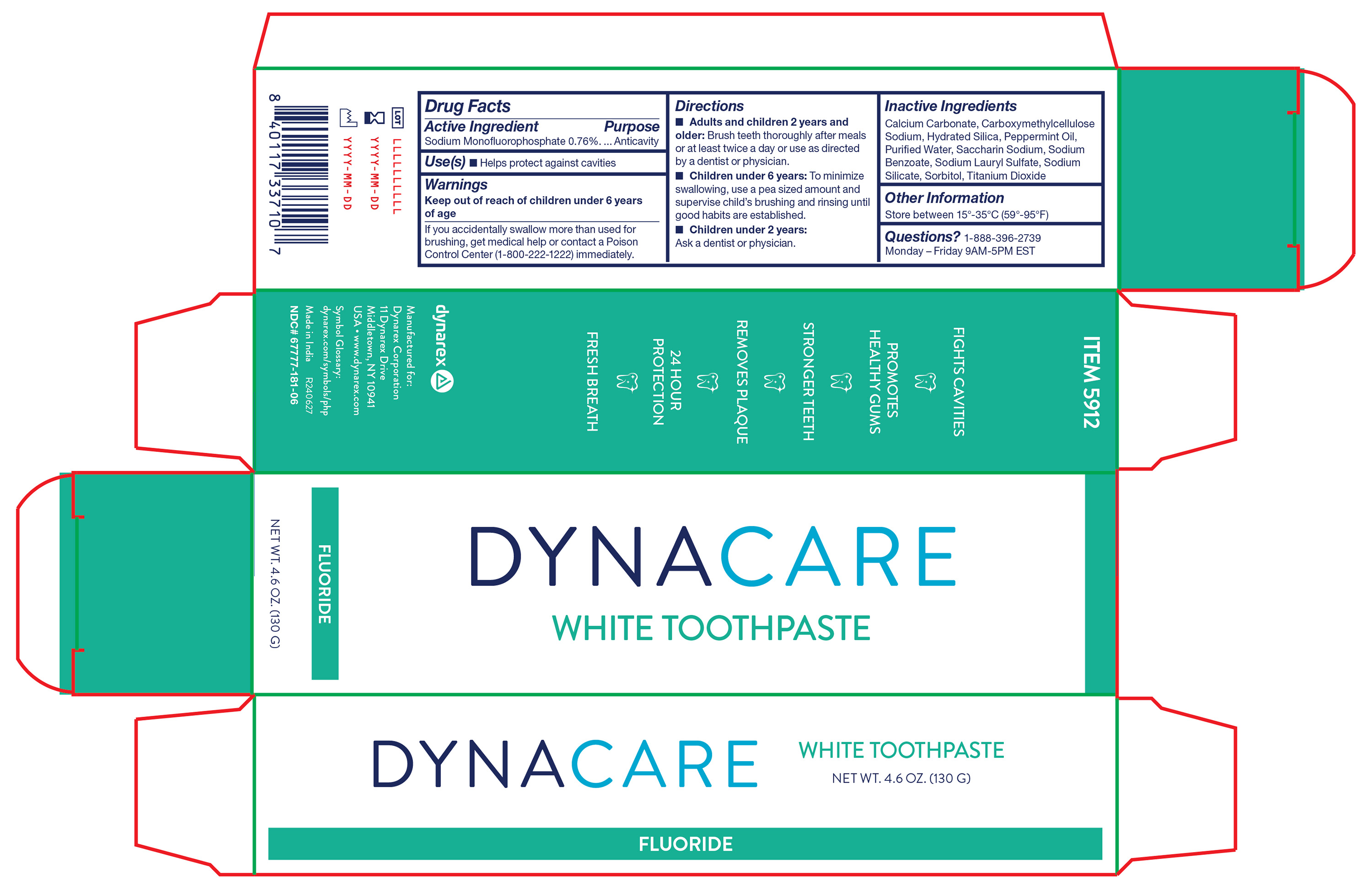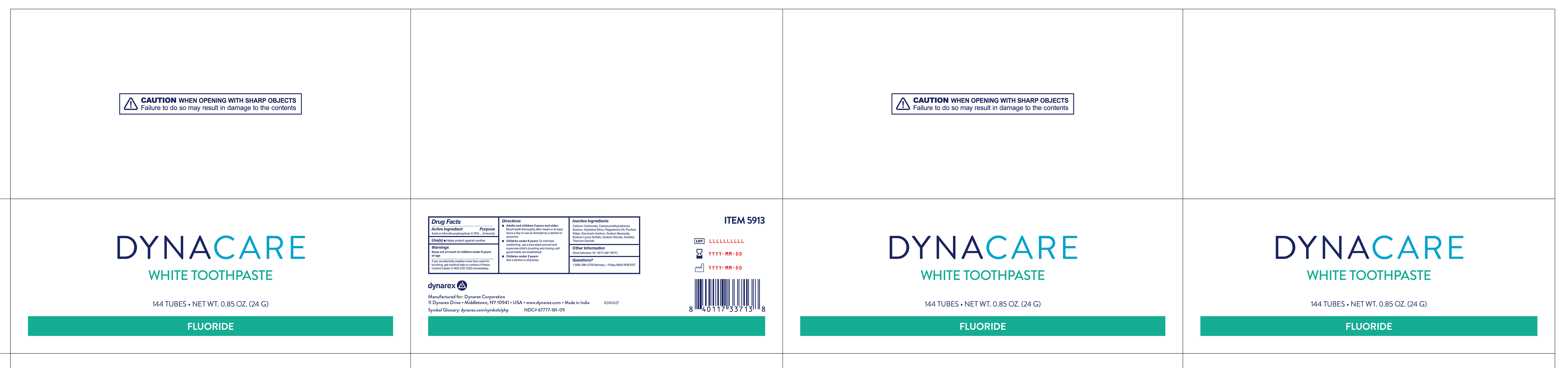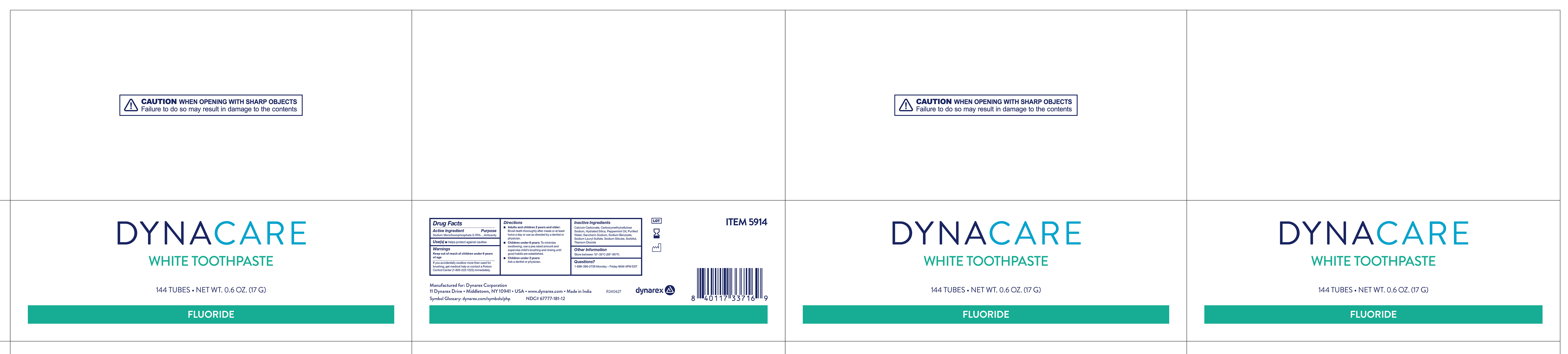 DRUG LABEL: Sodium Monofluorophosphate
NDC: 67777-181 | Form: PASTE
Manufacturer: Dynarex Corporation
Category: otc | Type: HUMAN OTC DRUG LABEL
Date: 20240703

ACTIVE INGREDIENTS: SODIUM MONOFLUOROPHOSPHATE 760 mg/1 g
INACTIVE INGREDIENTS: CALCIUM CARBONATE; SODIUM SILICATE; SORBITOL; HYDRATED SILICA; SACCHARIN SODIUM; SODIUM BENZOATE; WATER; PEPPERMINT OIL; CARBOXYMETHYLCELLULOSE SODIUM, UNSPECIFIED; SODIUM LAURYL SULFATE; TITANIUM DIOXIDE

5910 White Toothpaste
5911 White Toothpaste
5912 White Toothpast
5913 White Toothpaste
5914 White Toothpaste

Active Ingredient

Sodium Monofluorophosphate 0.76%

Purpose

Anticavity

Use(s)

Helps protect against cavities

Warnings

If you accidentally swallow more than used for brushing, get medical help or contact a Poison Control Center (1-800-222-1222) immediatley.

Keep out of reach of children

Keep out of reach of childen under 6 years of age

Directions

• Adults and children 2 years and older: Brush teeth thoroughly after meals or at least twice a day or use as directed by a dentist or physician.

• Children under 6 years: To minimize swallowing, use a pea sized amount and supervise child's brushing and rinsing until good habits are established.

• Children under 2 years: Ask a dentist or physician.

Inactive Ingredients

Calcium Carbonate, Carboxymethylcellulose Sodium, Hydrated Silica, Peppermint Oil, Purified Water, Saccharin Sodium, Sodium Benzoate, Sodium Lauryl Sulfate, Sodium Silicate, Sorbitol, Titanium Dioxide

Other Information

Store between 15°-35ºC (59º-95ºF)

Questions?

1-888-396-2739 Monday - Friday 9AM - 5PM EST

Label

5910 White Toothpaste

Label

5911 White Toothpaste

Label

5912 White Toothpaste

Label

5913 White Toothpaste

Label

5914 White Toothpaste